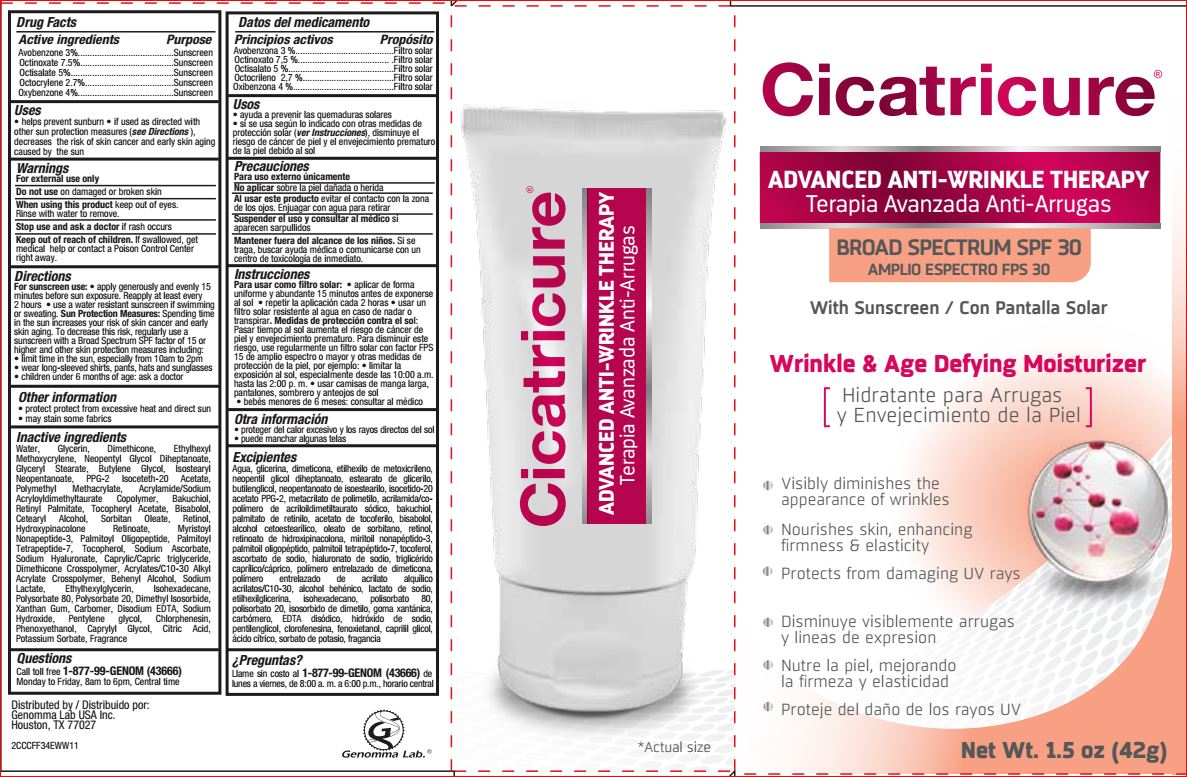 DRUG LABEL: Advanced Anti-Wrinkle Therapy
NDC: 50066-021 | Form: CREAM
Manufacturer: Genomma Lab
Category: otc | Type: HUMAN OTC DRUG LABEL
Date: 20190218

ACTIVE INGREDIENTS: AVOBENZONE 3 g/100 g; OCTINOXATE 7.5 g/100 g; OCTISALATE 5 g/100 g; OCTOCRYLENE 2.7 g/100 g; OXYBENZONE 4 g/100 g
INACTIVE INGREDIENTS: BUTYLENE GLYCOL; ISOSTEARYL NEOPENTANOATE; PPG-2 ISOCETETH-20 ACETATE; POLY(METHYL METHACRYLATE; 450000 MW); BAKUCHIOL; VITAMIN A PALMITATE; .ALPHA.-TOCOPHEROL ACETATE; LEVOMENOL; CETOSTEARYL ALCOHOL; SORBITAN MONOOLEATE; RETINOL; HYDROXYPINACOLONE RETINOATE; MYRISTOYL PENTAPEPTIDE-4; PALMITOYL TETRAPEPTIDE-7; TOCOPHEROL; SODIUM ASCORBATE; HYALURONATE SODIUM; MEDIUM-CHAIN TRIGLYCERIDES; CARBOMER INTERPOLYMER TYPE A (ALLYL SUCROSE CROSSLINKED); DOCOSANOL; SODIUM LACTATE; ETHYLHEXYLGLYCERIN; ISOHEXADECANE; POLYSORBATE 80; POLYSORBATE 20; DIMETHYL ISOSORBIDE; XANTHAN GUM; POLYACRYLIC ACID (8000 MW); EDETATE DISODIUM; SODIUM HYDROXIDE; PENTYLENE GLYCOL; CHLORPHENESIN; PHENOXYETHANOL; CAPRYLYL GLYCOL; CITRIC ACID MONOHYDRATE; POTASSIUM SORBATE; WATER; GLYCERIN; DIMETHICONE; ETHYLHEXYL METHOXYCRYLENE; NEOPENTYL GLYCOL DIHEPTANOATE; GLYCERYL STEARATE SE

ACTIVE INGREDIENT

Avobenzone 3%., Octinoxate 7.5%, Octisalate 5%,Octocrylene 2.7%,Oxybenzone 4%.

PURPOSE

Sunscreen

Uses

• helps prevent sunburn • if used as directed with other sun protection measures (see Directions), decreases the risk of skin cancer and early skin aging caused by the sun

Warnings

For external use only

Do not use on damaged or broken skin
When using this product keep out of eyes. Rinse with water to remove.
Stop use and ask a doctor if rash occurs.

Keep out of reach of children. If swallowed, get medical help or contact a Poison Control Center right away.

Directions

For sunscreen use: • apply generously and evenly 15 minutes before sun exposure. Reapply at least every 2 hours • use a water resistant sunscreen if swimming or sweating. Sun Protection Measures: Spending time in the sun increases your risk of skin cancer and early skin aging. To decrease this risk, regularly use a sunscreen with a Broad Spectrum SPF factor of 15 or higher and other skin protection measures including:
• limit time in the sun, especially from 10am to 2pm
• wear long-sleeved shirts, pants, hats and sunglasses
• children under 6 months of age: ask a doctor

Inactive ingredients

Water, Glycerin, Dimethicone, Ethylhexyl Methoxycrylene, Neopentyl Glycol Diheptanoate, Glyceryl Stearate, Butylene Glycol, Isostearyl Neopentanoate, PPG-2 Isoceteth-20 Acetate, Polymethyl Methacrylate, Acrylamide/Sodium Acryloyldimethyltaurate Copolymer, Bakuchiol, Retinyl Palmitate, Tocopheryl Acetate, Bisabolol, Cetearyl Alcohol, Sorbitan Oleate, Retinol, Hydroxypinacolone Retinoate, Myristoyl Nanapeptide-3, Palmitoyl Oligopeptide, Palmitoyl Tetrapeptide-7, Tocopherol, Sodium Ascorbate, Sodium Hyaluronate, Caprylic/Capric Triglyceride, Dimethicone Crosspolymer, Acrylates/C10-30 Alkyl Acrylate Crosspolymer, Behenyl Alcohol, Sodium Lactate, Ethylhexylglycerin, Isohexadecane, Polysorbate 80, Polysorbate 20, Dimethyl Isosorbide, Xanthan Gum, Carbomer, Disodium EDTA, Sodium Hydroxide, Pentylene Glycol, Chlorphenesin, Phenoxyethanol, Caprylyl Glycol, Citric Acid, Potassium Sorbate, Fragrance.